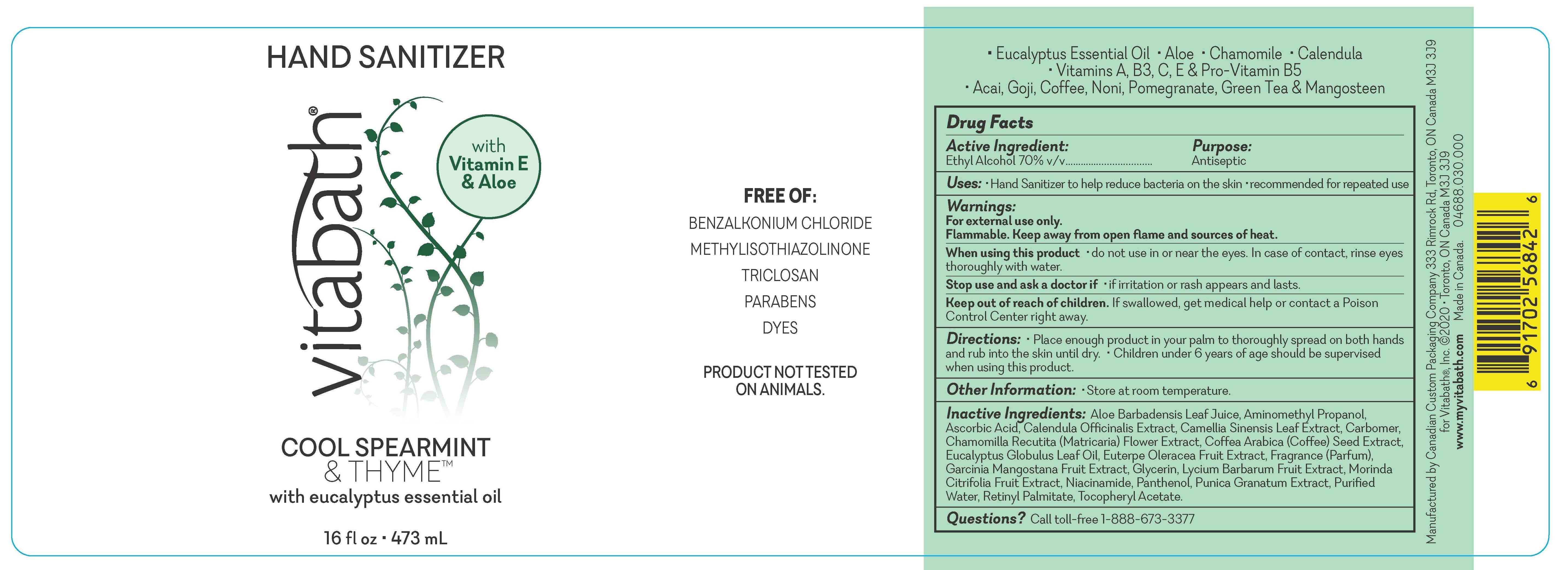 DRUG LABEL: Vitabath Hand Sanitizer Cool Spearmint and Thyme
NDC: 73172-008 | Form: GEL
Manufacturer: Vitabath Inc.
Category: otc | Type: HUMAN OTC DRUG LABEL
Date: 20200623

ACTIVE INGREDIENTS: ALCOHOL 70 mL/100 mL
INACTIVE INGREDIENTS: VITAMIN A PALMITATE; .ALPHA.-TOCOPHEROL ACETATE; ALOE VERA LEAF; AMINOMETHYLPROPANOL; ASCORBIC ACID; CALENDULA OFFICINALIS FLOWER; GREEN TEA LEAF; CARBOMER 1342; CHAMOMILE; ARABICA COFFEE BEAN; ACAI; FRAGRANCE LAVENDER & CHIA F-153480; GARCINIA MANGOSTANA FRUIT; GLYCERIN; EUCALYPTUS OIL; LYCIUM BARBARUM FRUIT; NONI FRUIT; NIACINAMIDE; PANTHENOL; PUNICA GRANATUM ROOT BARK; WATER

Vitabath Hand Sanitizer Cool Spearment and Thyme

Active Ingredient

Ethyl Alcohol 63% w/w

Purpose

Antiseptic

Uses

• Hand Sanitizer to help reduce bacteria on the skin • recommended for repeated use

Warnings

For external use only.
Flammable. Keep away from open flame and sources of heat.

When using this product • do not use in or near the eyes. In case of contact, rinse eyes thoroughtly with water.

Stop use and ask a doctor if • if irritation or rash appears and lasts.

Keep out of reach of children. If swallowed, get medical help or contact a Poison Control Center
right away..

Directions

Directions • Place enough product in your palm to thoroughtly spread on both hands and rub into the skin until dry • Children under 6 years of age should be supervised when using this product.

OTHER INFORMATION

Other Information: • Store at room temperature.

Inactive Ingredients

Inactive Ingredients: Aloe Barbadensis Leaf Juice, Aminomethyl Propanol, Ascorbic Acid, Calendula Officinalis Extract, Camellia Sinensis Leaf Extract, Carbomer, Chamomilla Recutita (Matricaria) Flower Extract, Coffea Arabica (Coffee) Seed Extract, Eucalyptus Globulus Leaf Oil, Euterpe Oleracea Fruit Extract, Fragrance (Parfum), Garcinia Mangostana Fruit Extract, Glycerin, Lycium Barbarum Fruit Extract, Morinda Citrifolia Fruit Extract, Niacinamide, Panthenol, Punica Granatum Extract, Purified Water, Retinyl Palmitate, Tocopheryl Acetate.

Questions? Call toll-free 1-888-673-3377